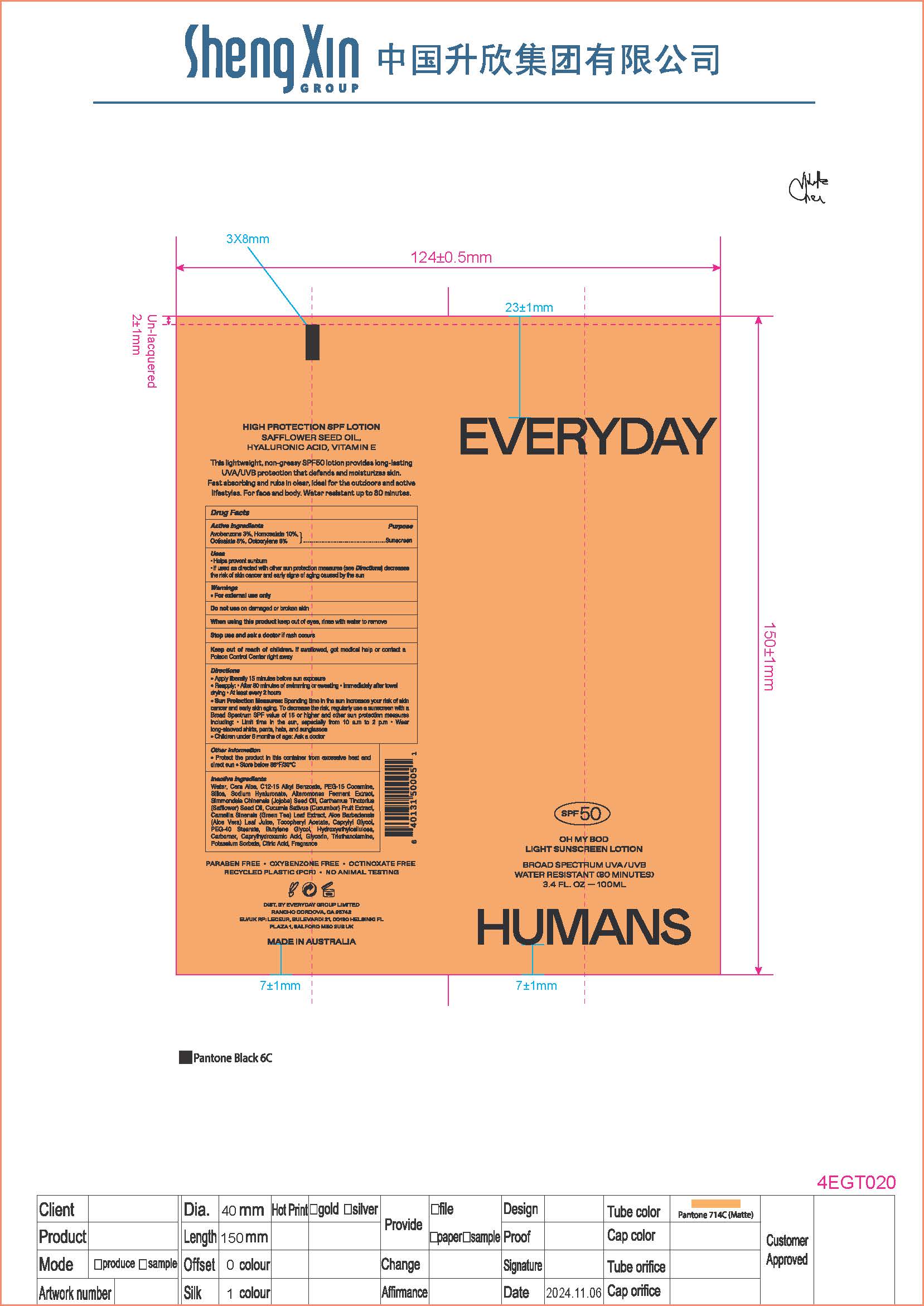 DRUG LABEL: Oh My Bod Light Sunscreen Broad Spectrum SPF 50
NDC: 70157-033 | Form: LOTION
Manufacturer: Baxter Laboratories Pty. Ltd.
Category: otc | Type: HUMAN OTC DRUG LABEL
Date: 20250912

ACTIVE INGREDIENTS: HOMOSALATE 10 g/100 mL; OCTISALATE 5 g/100 mL; OCTOCRYLENE 8 g/100 mL; AVOBENZONE 3 g/100 mL
INACTIVE INGREDIENTS: SILICA; BUTYLENE GLYCOL; CAPRYLHYDROXAMIC ACID; GREEN TEA LEAF; WHITE WAX; PEG-15 COCAMINE; HYDROXYETHYLCELLULOSE; ALOE BARBADENSIS LEAF JUICE; PEG-40 STEARATE; CAPRYLYL GLYCOL; SODIUM HYALURONATE; CARBOMER; GLYCERIN; CITRIC ACID; ALTEROMONAS MACLEODII POLYSACCHARIDES; CARTHAMUS TINCTORIUS (SAFFLOWER) SEED OIL; TRIETHANOLAMINE; .ALPHA.-TOCOPHEROL ACETATE; POTASSIUM SORBATE; WATER; JOJOBA OIL; CUCUMIS SATIVUS (CUCUMBER) FRUIT; C12-15 ALKYL BENZOATE

Oh My Bod Light Sunscreen Broad Spectrum SPF 50

Active Ingredients Purpose

Avobenzone 3% Sunscreen

Homosalate 10% Sunscreen

Octisalate 5% Sunscreen

Octocrylene 8% Sunscreen

Uses

- Helps prevent sunburn
- If used as directed with other sun protection measures (see Directions), decreases the risk of skin cancer and early skin aging caused by the sun.

Keep out of reach of children. If swallowed, get medical help or contact a Poison Control Center right away.

Stop use and ask a doctor if rash occurs.

Warnings

- For external use only
- Do not use on damaged or broken skin
- When using this product keep out of eyes, rinse with water to remove

Directions

- Apply liberally 15 minutes before sun exposure.
- Reapply
- After 80 minutes of swimming or sweating
- Immediately after towel drying
- At least every 2 hours

Sun Protection Measures. Spending time in the sun increases your risk of skin cancer and early skin aging. To decrease this risk, regularly use a sunscreen with a Broad Spectrum SPF value of 15 or higher and other sun protection measures including:

- Limit time in the sun, especially from 10 a.m.- 2 p.m.
- Wear long-sleeved shirts, pants, hats, and sunglasses.
- Children under 6 months: Ask a doctor.

Inactive ingredients

Water, Cera Alba, C12-15 Alkyl Benzoate,PEG-15 Cocamine, Silica, Sodium Hyaluronate, Alteromonas Ferment Extract, Simmondsia Chinensis (Jojoba) Seed Oil, Carthamus Tinctorius (Safflower) Seed Oil, Cucumis Sativus (cucumber) Fruit Extract, Camellia Sinensis (Green Tea) Leaf Extract, Aloe Barbadensis (Aloe Vera) Leaf Juice, Tocopheryl Acetate, Caprylyl Glycol, PEG-40 Stearate, Butylene Glycol, Hydroxyethylcellulose, Carbomer, Caprylhydroxamic Acid, Glycerin, Triethanolamine, Potassium Sorbate, Citric acid, Fragrance.

Other information

- Protect the product in this conainer from excessive heat and direct sun
- Store below 86ºF/30ºC

PACKAGE LABEL

Everyday Humans

SPF 50

Oh my Bod

Light Sunscreen Lotion

Broad Spectrum UVA/UVB

Water Resistant (80 Minutes)

3.4 FL. OZ - 100 ML